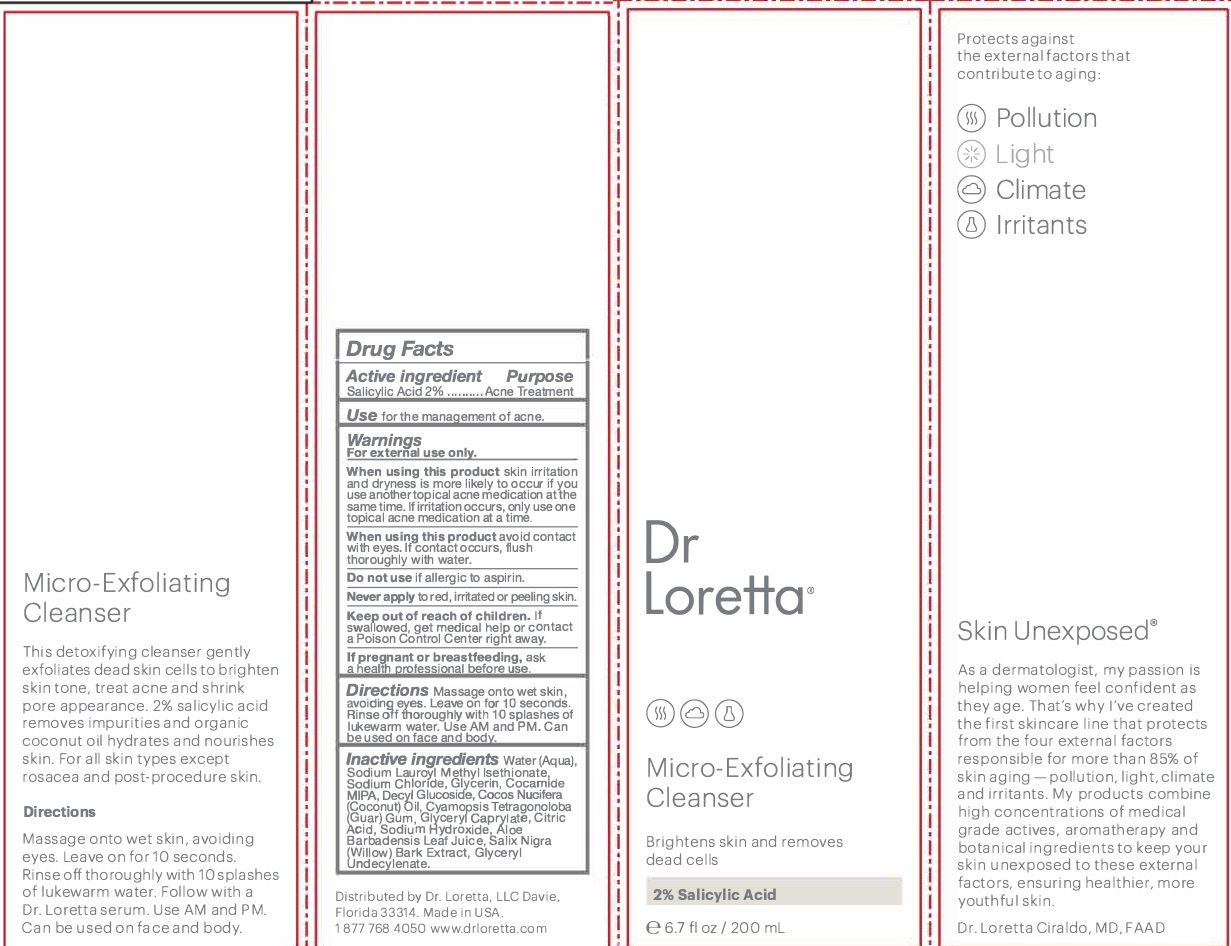 DRUG LABEL: Micro Exfoliating Cleanser
NDC: 71501-1901 | Form: LIQUID
Manufacturer: Dr. Loretta, LLC
Category: otc | Type: HUMAN OTC DRUG LABEL
Date: 20250806

ACTIVE INGREDIENTS: SALICYLIC ACID 20 mg/1 mL
INACTIVE INGREDIENTS: WATER; SODIUM CHLORIDE; SODIUM LAUROYL METHYL ISETHIONATE; GLYCERIN; COCO MONOISOPROPANOLAMIDE; DECYL GLUCOSIDE; COCONUT OIL; GUAR GUM; ALOE VERA LEAF; SALIX NIGRA BARK; GLYCERYL CAPRYLATE/CAPRATE; CITRIC ACID MONOHYDRATE; SODIUM HYDROXIDE; GLYCERYL 1-UNDECYLENATE

Micro-Exfoliating Cleanser

PURPOSE

Acne treatment

WARNINGS

For external use only

Keep out of reach of children.

INACTIVE INGREDIENT

Water,

Sodium Lauroyl Methyl Isethionate

Sodium Chloride

Glycerin Cocamide MIPA

Decyl Glucoside

Cocos Nucifera (Coconut) Oil

Cyamopsis Tetragonoloba (Guar) Gum

Aloe Barbadensis Leaf Juice

Salix Nigra (Willow) Bark Extract

Glyceryl Caprylate

CitricAcid

Sodium Hydroxide

Glyceryl Undecylenate

ACTIVE INGREDIENT

Salicylic Acid 2.0%

INDICATIONS AND USAGE

Acne Treatment

DOSAGE AND ADMINISTRATION

Topical